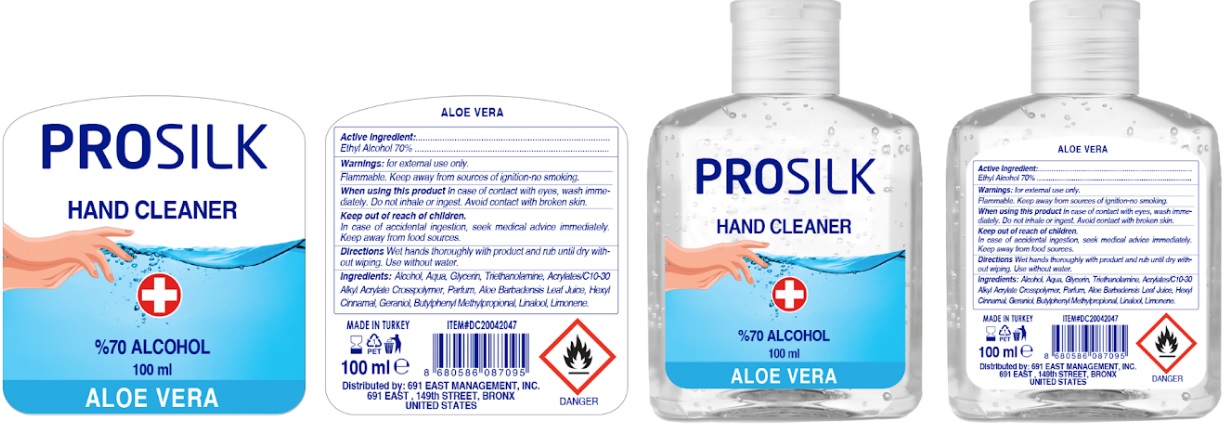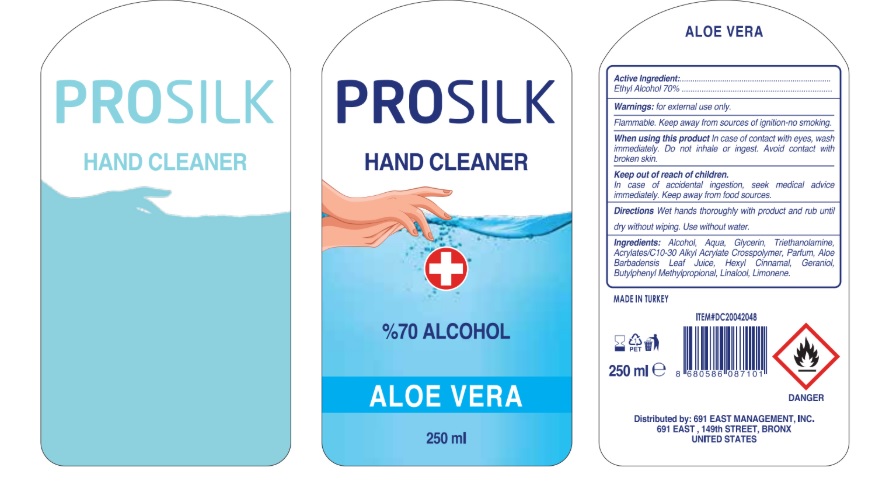 DRUG LABEL: Prosilk  hand Sanitizer
NDC: 78242-001 | Form: GEL
Manufacturer: DIAMO KOZMETIK SANAYI IC VE DIS TICARET LIMITED SIRKETI
Category: otc | Type: HUMAN OTC DRUG LABEL
Date: 20200521

ACTIVE INGREDIENTS: ALCOHOL 70 mL/100 mL
INACTIVE INGREDIENTS: WATER; .ALPHA.-HEXYLCINNAMALDEHYDE; PROPYLENE GLYCOL; CARBOMER INTERPOLYMER TYPE A (ALLYL SUCROSE CROSSLINKED); GLYCERIN; ALOE VERA LEAF; AMINOMETHYLPROPANOL; PEG-40 CASTOR OIL; BUTYLPHENYL METHYLPROPIONAL; LINALOOL, (+/-)-; LIMONENE, (+/-)-; TROLAMINE

PROSILK Hand sanitizer Aloe vera

Drug Facts

Active Ingredient

Ethyl Alcohol, 70%..................

Purpose

Antiseptic

Use

Flammable . keep away from sources of ignition-no smoking.

Warnings

for external use only.

Uses

In cases of contact with eyes, wash immediately.

Do not innhale or ingest.

Avoid contct with beoken skin.

KEEP OUT OF REACH OF CHILDREN

In cases of accidental ingestion,seek medical advice immediately.

Keepaway from food sources.

Directions

Wet hands thoroughly with product and rub until dry without wiping.

Use without water.

Inactive Ingredients

Alcohol,Aqua,Glycerin,trinethanolamine,Acrylates/C10-30 Alkyl Acrylare Crosspolymer, Parfum, Aloe Barbadensis Leaf Juice,HexylCinnamal,

Geraniol,Butypheny methlypropinal, Linalool, Limonene.

Please see label on the container.